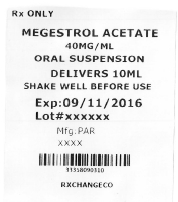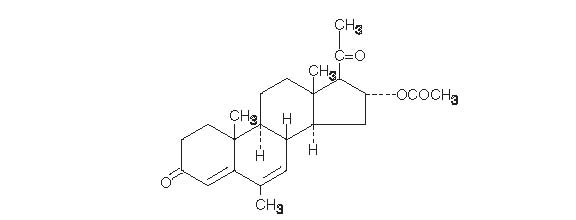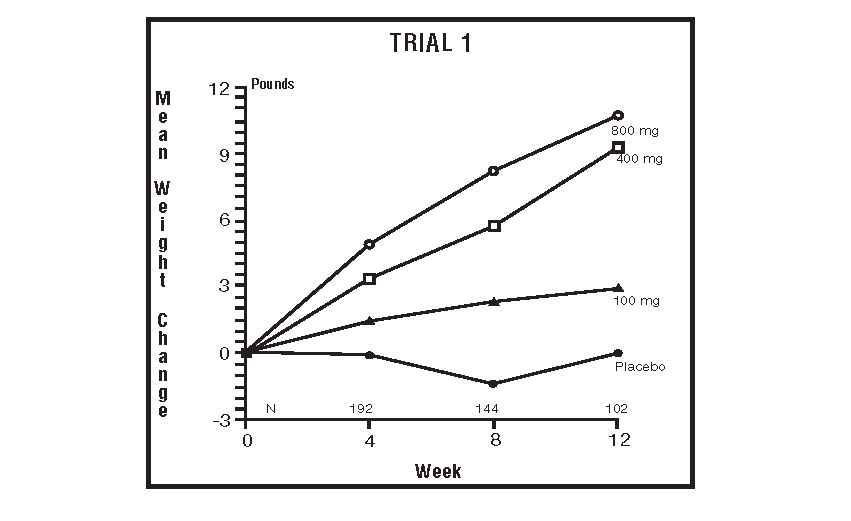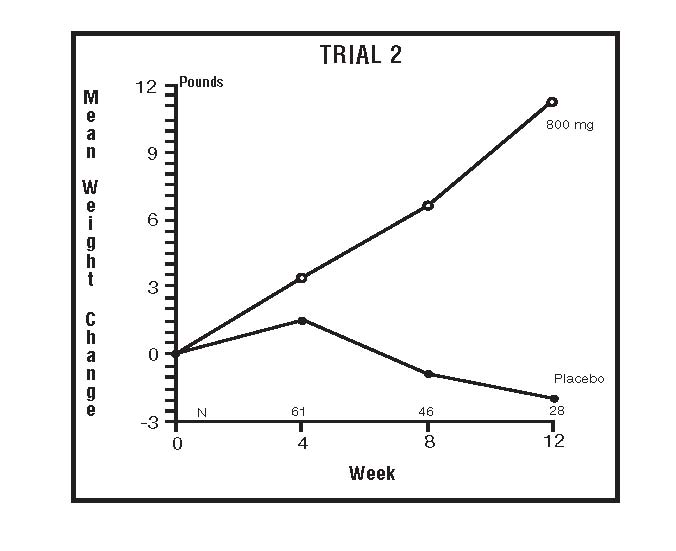 DRUG LABEL: Megestrol Acetate
NDC: 33358-903 | Form: SUSPENSION
Manufacturer: Rxchange Co
Category: prescription | Type: HUMAN PRESCRIPTION DRUG LABEL
Date: 20160908

ACTIVE INGREDIENTS: MEGESTROL ACETATE 40 mg/1 mL

DESCRIPTION

Megestrol acetate oral suspension, USP contains megestrol acetate, a synthetic derivative of the naturally occurring steroid hormone, progesterone. Megestrol acetate is a white, crystalline solid chemically designated as 17-Hydroxy-6-methylpregna-4,6-diene-3,20-dione acetate. Solubility at 37°C in water is 2 mcg per mL, solubility in plasma is 24 mcg per mL. Its molecular weight is 384.52.

The chemical formula is C24H32O4 and the structural formula is represented as follows:

Megestrol acetate oral suspension is supplied as an oral suspension containing 40 mg of micronized megestrol acetate per mL.

Megestrol acetate oral suspension contains the following inactive ingredients: alcohol (max 0.06% v/v from flavor), artificial lime flavor, citric acid monohydrate, docusate sodium, glycerin, natural and artificial lemon flavor, purified water, sodium benzoate, sodium citrate dihydrate, sucrose and xanthan gum.

Megestrol acetate oral suspension, 40 mg/mL complies with USP Dissolution Test 2.

CLINICAL PHARMACOLOGY

Several investigators have reported on the appetite enhancing property of megestrol acetate and its possible use in cachexia. The precise mechanism by which megestrol acetate produces effects in anorexia and cachexia is unknown at the present time.

There are several analytical methods used to estimate megestrol acetate plasma concentrations, including gas chromatography-mass fragmentography (GC-MF), high pressure liquid chromatography (HPLC) and radioimmunoassay (RIA). The GC-MF and HPLC methods are specific for megestrol acetate and yield equivalent concentrations. The RIA method reacts to megestrol acetate metabolites and is, therefore, non-specific and indicates higher concentrations than the GC-MF and HPLC methods. Plasma concentrations are dependent, not only on the method used, but also on intestinal and hepatic inactivation of the drug, which may be affected by factors such as intestinal tract motility, intestinal bacteria, antibiotics administered, body weight, diet and liver function.

The major route of drug elimination in humans is urine. When radiolabeled megestrol acetate was administered to humans in doses of 4 to 90 mg, the urinary excretion within 10 days ranged from 56.5 to 78.4% (mean 66.4%) and fecal excretion ranged from 7.7 to 30.3% (mean 19.8%). The total recovered radioactivity varied between 83.1 and 94.7% (mean 86.2%). Megestrol acetate metabolites which were identified in urine constituted 5 to 8% of the dose administered. Respiratory excretion as labeled carbon dioxide and fat storage may have accounted for at least part of the radioactivity not found in urine and feces.

Plasma steady state pharmacokinetics of megestrol acetate were evaluated in 10 adult, cachectic male patients with acquired immunodeficiency syndrome (AIDS) and an involuntary weight loss greater than 10% of baseline. Patients received single oral doses of 800 mg/day of megestrol acetate oral suspension for 21 days. Plasma concentration data obtained on day 21 were evaluated for up to 48 hours past the last dose.

Mean (±1SD) peak plasma concentration (Cmax) of megestrol acetate was 753 (±539) ng/mL. Mean area under the concentration time-curve (AUC) was 10476 (±7788) ng x hr/mL. Median Tmax value was five hours. Seven of 10 patients gained weight in three weeks.

Additionally, 24 adult, asymptomatic HIV seropositive male subjects were dosed once daily with 750 mg of megestrol acetate oral suspension. The treatment was administered for 14 days. Mean Cmax and AUC values were 490 (±238) ng/mL and 6779 (±3048) hr x ng/mL, respectively. The median Tmax value was three hours. The mean Cmin value was 202 (±101) ng/mL. The mean % of fluctuation value was 107 (±40).

The effect of food on the bioavailability of megestrol acetate oral suspension has not been evaluated.

INDICATIONS AND USAGE

Megestrol acetate oral suspension, USP is indicated for the treatment of anorexia, cachexia, or an unexplained, significant weight loss in patients with a diagnosis of acquired immunodeficiency syndrome (AIDS).

CONTRAINDICATIONS

History of hypersensitivity to megestrol acetate or any component of the formulation. Known or suspected pregnancy.

WARNINGS

Megestrol acetate may cause fetal harm when administered to a pregnant woman. For animal data on fetal effects, (see PRECAUTIONS: Carcinogenesis, Mutagenesis, Impairment of Fertility: Impairment of Fertility). There are no adequate and well-controlled studies in pregnant women. If this drug is used during pregnancy, or if the patient becomes pregnant while taking (receiving) this drug, the patient should be apprised of the potential hazard to the fetus. Women of childbearing potential should be advised to avoid becoming pregnant.

Megestrol acetate is not intended for prophylactic use to avoid weight loss.

(See also PRECAUTIONS: Carcinogenesis, Mutagenesis, and Impairment of Fertility section.)

The glucocorticoid activity of megestrol acetate oral suspension has not been fully evaluated. Clinical cases of new onset diabetes mellitus, exacerbation of pre-existing diabetes mellitus, and overt Cushing’s Syndrome have been reported in association with the chronic use of megestrol acetate. In addition, clinical cases of adrenal insufficiency have been observed in patients receiving or being withdrawn from chronic megestrol acetate therapy in the stressed and non-stressed state. Furthermore, adrenocorticotropin (ACTH) stimulation testing has revealedthe frequent occurrence of asymptomatic pituitary-adrenal suppression in patients treated with chronic megestrol acetate therapy. Therefore, the possibility of adrenal insufficiency should be considered in any patient receiving or being withdrawn from chronic megestrol acetate therapy who presents with symptoms and/or signs suggestive of hypoadrenalism (e.g., hypotension, nausea, vomiting, dizziness, or weakness) in either the stressed or non-stressed state. Laboratory evaluation for adrenal insufficiency and consideration of replacement or stress doses of a rapidly acting glucocorticoid are strongly recommended in such patients. Failure to recognize inhibition of the hypothalamic-pituitary-adrenal axis may result in death. Finally, in patients who are receiving or being withdrawn from chronic megestrol acetate therapy, consideration should be given to the use of empiric therapy with stress doses of a rapidly acting glucocorticoid in conditions of stress or serious intercurrent illness (e.g., surgery, infection).

OVERDOSAGE

No serious unexpected side effects have resulted from studies involving megestrol acetate oral suspension administered in dosages as high as 1200 mg/day. In post-marketing experience, limited reports of overdose have been received. Signs and symptoms reported in the context of overdose included diarrhea, nausea, abdominal pain, shortness of breath, cough, unsteady gait, listlessness, and chest pain. There is no specific antidote for overdose with megestrol acetate oral suspension. In case of overdose, appropriate supportive measures should be taken. Megestrol acetate has not been tested for dialyzability, however, due to its low solubility it is postulated that dialysis would not be an effective means of treating overdose

DOSAGE AND ADMINISTRATION

The recommended adult initial dosage of megestrol acetate oral suspension is 800 mg/day (20 mL/day). Shake container well before using.

In clinical trials evaluating different dose schedules, daily doses of 400 and 800 mg/day were found to be clinically effective.

HOW SUPPLIED

Megestrol acetate oral suspension, USP is available as a milky white, lemon-lime flavored oral suspension containing 40 mg of micronized megestrol acetate per mL.

DESCRIPTION OF CLINICAL STUDIES

The clinical efficacy of megestrol acetate oral suspension was assessed in two clinical trials. One was a multicenter, randomized, double-blind, placebo-controlled study comparing megestrol acetate (MA) at doses of 100 mg, 400 mg, and 800 mg per day versus placebo in AIDS patients with anorexia/cachexia and significant weight loss. Of the 270 patients entered on study, 195 met all inclusion/exclusion criteria, had at least two additional post baseline weight measurements over a 12 week period or had one post baseline weight measurement but dropped out for therapeutic failure. The percent of patients gaining five or more pounds at maximum weight gain in 12 study weeks was statistically significantly greater for the 800 mg (64%) and 400 mg (57%) MA-treated groups than for the placebo group (24%). Mean weight increased from baseline to last evaluation in 12 study weeks in the 800 mg MA-treated group by 7.8 pounds, the 400 mg MA group by 4.2 pounds, the 100 mg MA group by 1.9 pounds and decreased in the placebo group by 1.6 pounds. Mean weight changes at 4, 8 and 12 weeks for patients evaluable for efficacy in the two clinical trials are shown graphically. Changes in body composition during the 12 study weeks as measured by bioelectrical impedance analysis showed increases innon-water body weight in the MA-treated groups (see CLINICAL STUDIES table). In addition, edema developed or worsened in only 3 patients.

Greater percentages of MA-treated patients in the 800 mg group (89%), the 400 mg group (68%) and the 100 mg group (72%), than in the placebo group (50%), showed an improvement in appetite at last evaluation during the 12 study weeks. A statistically significant difference was observed between the 800 mg MA-treated group and the placebo group in the change in caloric intake from baseline to time of maximum weight change. Patients were asked to assess weight change, appetite, appearance, and overall perception of well-being in a 9 question survey. At maximum weight change only the 800 mg MA-treated group gave responses that were statistically significantly more favorable to all questions when compared to the placebo-treated group. A dose response was noted in the survey with positive responses correlating with higher dose for all questions.

The second trial was a multicenter, randomized, double-blind, placebo-controlled study comparing megestrol acetate 800 mg/day versus placebo in AIDS patients with anorexia/cachexia and significant weight loss. Of the 100 patients entered on study, 65 met all inclusion/exclusion criteria, had at least two additional post baseline weight measurements over a 12 week period or had one post baseline weight measurement but dropped out for therapeutic failure. Patients in the 800 mg MA-treated group had a statistically significantly larger increase in mean maximum weight change than patients in the placebo group. From baseline to study week 12, mean weight increased by 11.2 pounds in the MA-treated group and decreased 2.1 pounds in the placebo group. Changes in body composition as measured by bioelectrical impedance analysis showed increases in non-water weight in the MA-treated group (see CLINICAL STUDIES table). No edema was reported in the MA-treated group. A greater percentage of MA-treated patients (67%) than placebo-treated patients (38%) showed an improvement in appetite at last evaluation during the 12 study weeks; this difference was statistically significant. There were no statistically significant differences between treatment groups in mean caloric change or in daily caloric intake at time to maximum weight change. In the same 9 question survey referenced in the first trial, patients’ assessments of weight change, appetite, appearance, and overall perception of well-being showed increases in mean scores in MA-treated patients as compared to the placebo group.

In both trials, patients tolerated the drug well and no statistically significant differences were seen between the treatment groups with regard to laboratory abnormalities, , new opportunistic infections, lymphocyte counts, T4 counts, T8 counts, or skin reactivity tests (see ADVERSE REACTIONS).

The following figures are the results of mean weight changes for patients evaluable for efficacy in trials 1 and 2

MEGESTROL ACETATE 40mg/mL SUSPENSION

NDC 33358-903-05 - 5mL Cup

NDC 33358-903-10 - 10mL Cup

NDC 33358-903-20 - 20mL Cup